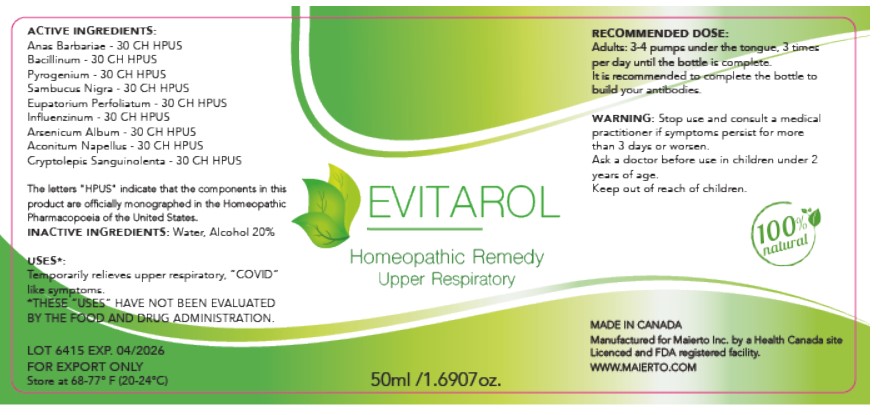 DRUG LABEL: Evitarol
NDC: 81762-101 | Form: LIQUID
Manufacturer: Maierto Inc
Category: homeopathic | Type: HUMAN OTC DRUG LABEL
Date: 20210426

ACTIVE INGREDIENTS: BOVINE TUBERCULIN 30 [hp_C]/30 [hp_C]; ACONITUM NAPELLUS WHOLE 30 [hp_C]/30 [hp_C]; CRYPTOLEPIS SANGUINOLENTA WHOLE 30 [hp_C]/30 [hp_C]; CAIRINA MOSCHATA HEART/LIVER AUTOLYSATE 30 [hp_C]/30 [hp_C]; INFLUENZA A VIRUS A/HONG KONG/2671/2019 (H3N2) NIB-121 NEURAMINIDASE ANTIGEN (UV, FORMALDEHYDE INACTIVATED) 30 [hp_C]/30 [hp_C]; INFLUENZA B VIRUS B/WASHINGTON/02/2019 ANTIGEN (FORMALDEHYDE INACTIVATED) 30 [hp_C]/30 [hp_C]; SAMBUCUS NIGRA FLOWERING TOP 30 [hp_C]/30 [hp_C]; ARSENIC TRIOXIDE 30 [hp_C]/30 [hp_C]; INFLUENZA A VIRUS A/GUANGDONG-MAONAN/SWL1536/2019 CNIC-1909 (H1N1) ANTIGEN (FORMALDEHYDE INACTIVATED) 30 [hp_C]/30 [hp_C]; RANCID BEEF 30 [hp_C]/30 [hp_C]; INFLUENZA B VIRUS B/PHUKET/3073/2013 ANTIGEN (FORMALDEHYDE INACTIVATED) 30 [hp_C]/30 [hp_C]; EUPATORIUM PERFOLIATUM FLOWERING TOP 30 [hp_C]/30 [hp_C]
INACTIVE INGREDIENTS: WATER; ALCOHOL

Active Ingredients

Anas Barbariae 30CH HPUS

Bacillinum 30CH HPUS

Pyrogenium 30CH HPUS

Sambucus Nigra 30CH HPUS

Eupatorium Perfoliatum 30CH HPUS

Influenzinum 30CH

Arsenicum Album 30CH HPUS

Aconitum Napellus 30CH HPUS

Cryptolepis Sanguinolenta 30CH HPUS

The letters "HPUS" indicate that the components in this product are officially monographed in the Homeopathic Pharmacopoeia of the United States.

PURPOSE

Anas Barbariae 30CH HPUS ..... reduces the duration of and severity of flu-like symptoms

Bacillinum 30CH HPUS ….. helps in treatment of tuberculosis and relief from other respiratory disorders like asthma and bronchitis

Pyrogenium 30CH HPUS ….. helps promote and maintain a healthy upper respiratory tract, and temporarily alleviates symptoms associated with general nasal and sinus congestion.

Sambucus Nigra 30CH HPUS ….. boosts immune system, and helps prevent and ease cold and flu-like symptoms

Eupatorium Perfoliatum 30CH HPUS ….. helps to reduce fever, and relieves stiffness and bone pain

Influenzinum 30CH HPUS …. prevention and relief of flu-like symptoms

Arsenicum Album 30CH HPUS ….. reduces inflammation in body

Aconitum Napellus 30CH HPUS ….. alleviates fever and chills

Cryptolepis Sanguinolenta 30CH HPUS ….. antibacterial and anti-inflammatory activity

Uses*

Temporarily relieves upper respiratory, COVID like symptoms.

*THESE “USES” HAVE NOT BEEN EVALUATED BY THE FOOD AND DRUG ADMINISTRATION.

DOSAGE AND ADMINISTRATION

Adults: 3 - 4 pumps under the tongue, 3 times per day until the bottle is complete. It is recommended to complete the bottle to build your antibodies.

Warning

Stop use and consult a medical practitioner if symptoms persist for more than 3 days or worsen.

Ask a doctor before use in children under 2 years of age.

Keep out of reach of children.

Inactive Ingredients: Water, Alcohol 20%

PACKAGE LABEL

Evitarol

Homeopathic Remedy

Upper Respiratory